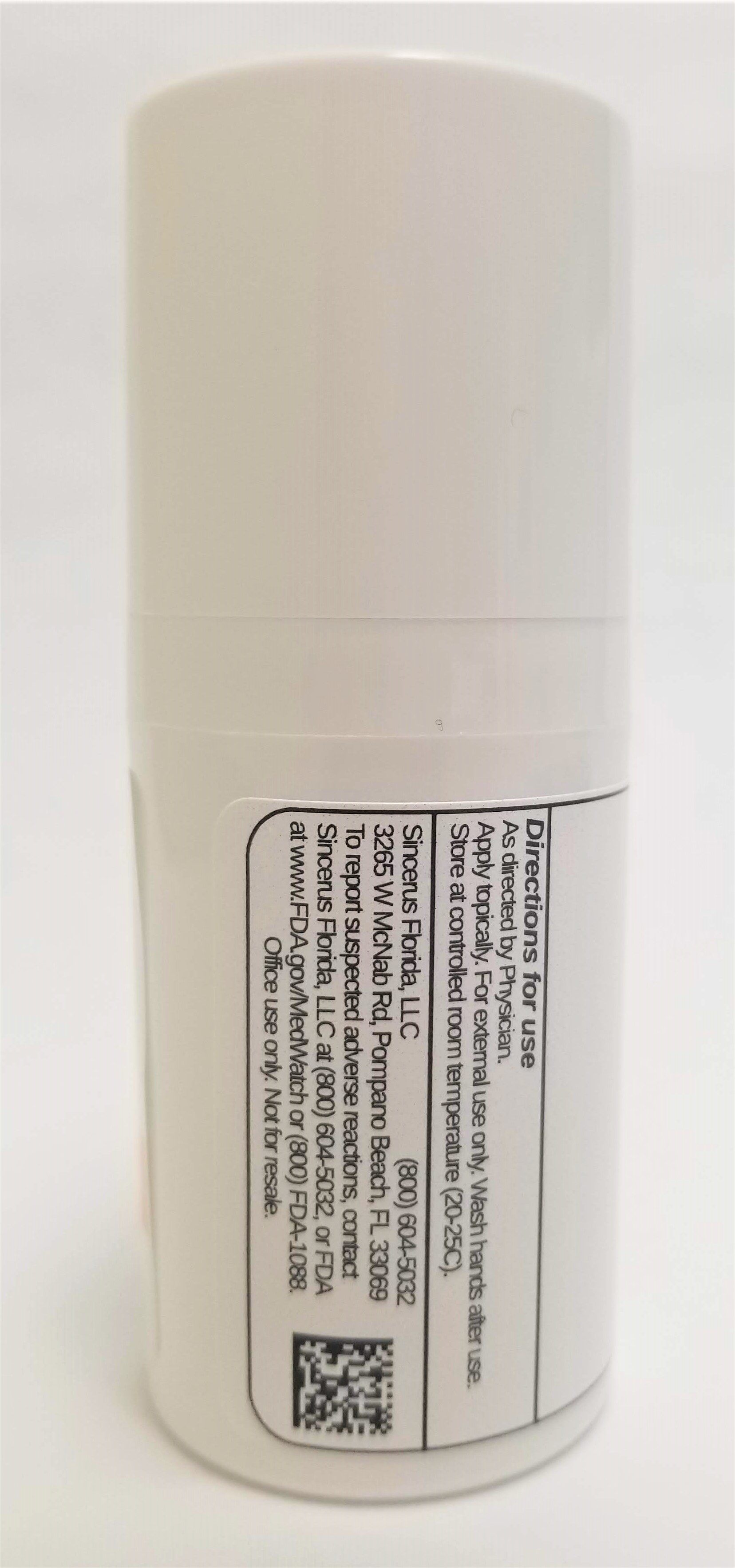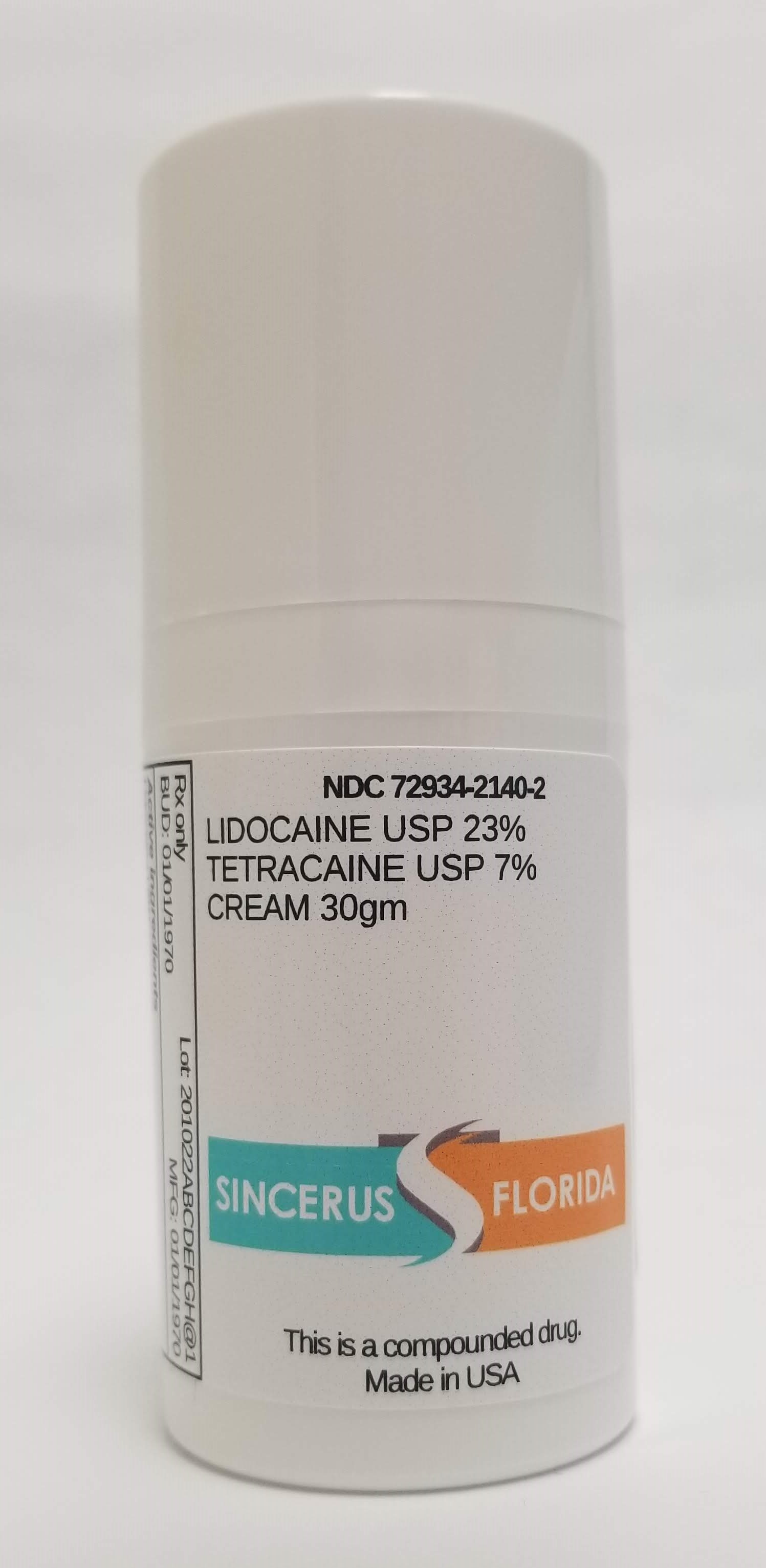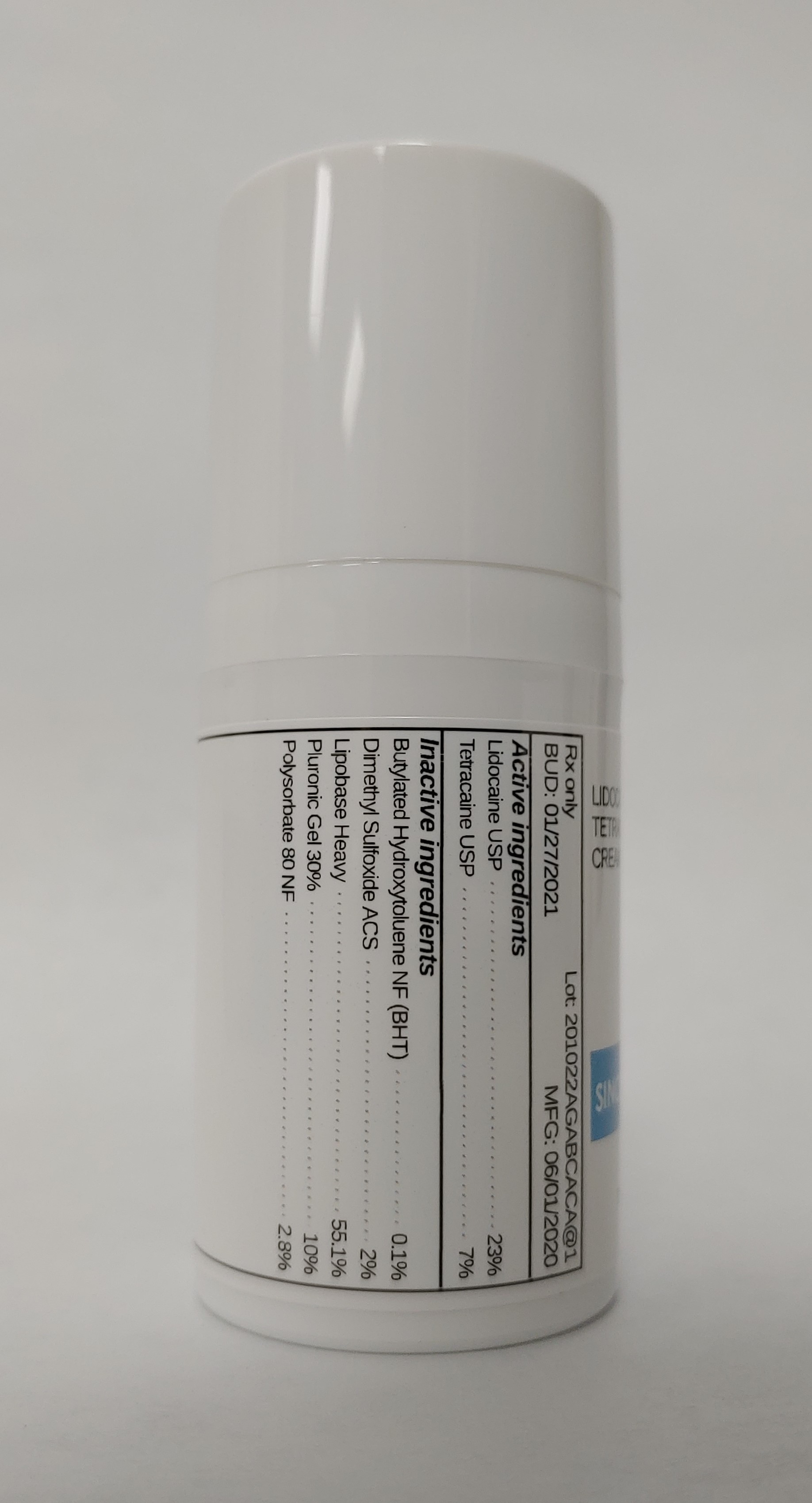 DRUG LABEL: LIDOCAINE 23% / TETRACAINE 7%
NDC: 72934-2140 | Form: CREAM
Manufacturer: Sincerus Florida, LLC
Category: prescription | Type: HUMAN PRESCRIPTION DRUG LABEL
Date: 20200604

ACTIVE INGREDIENTS: TETRACAINE 7 g/100 g; LIDOCAINE 23 g/100 g

LIDOCAINE 23% / TETRACAINE 7%